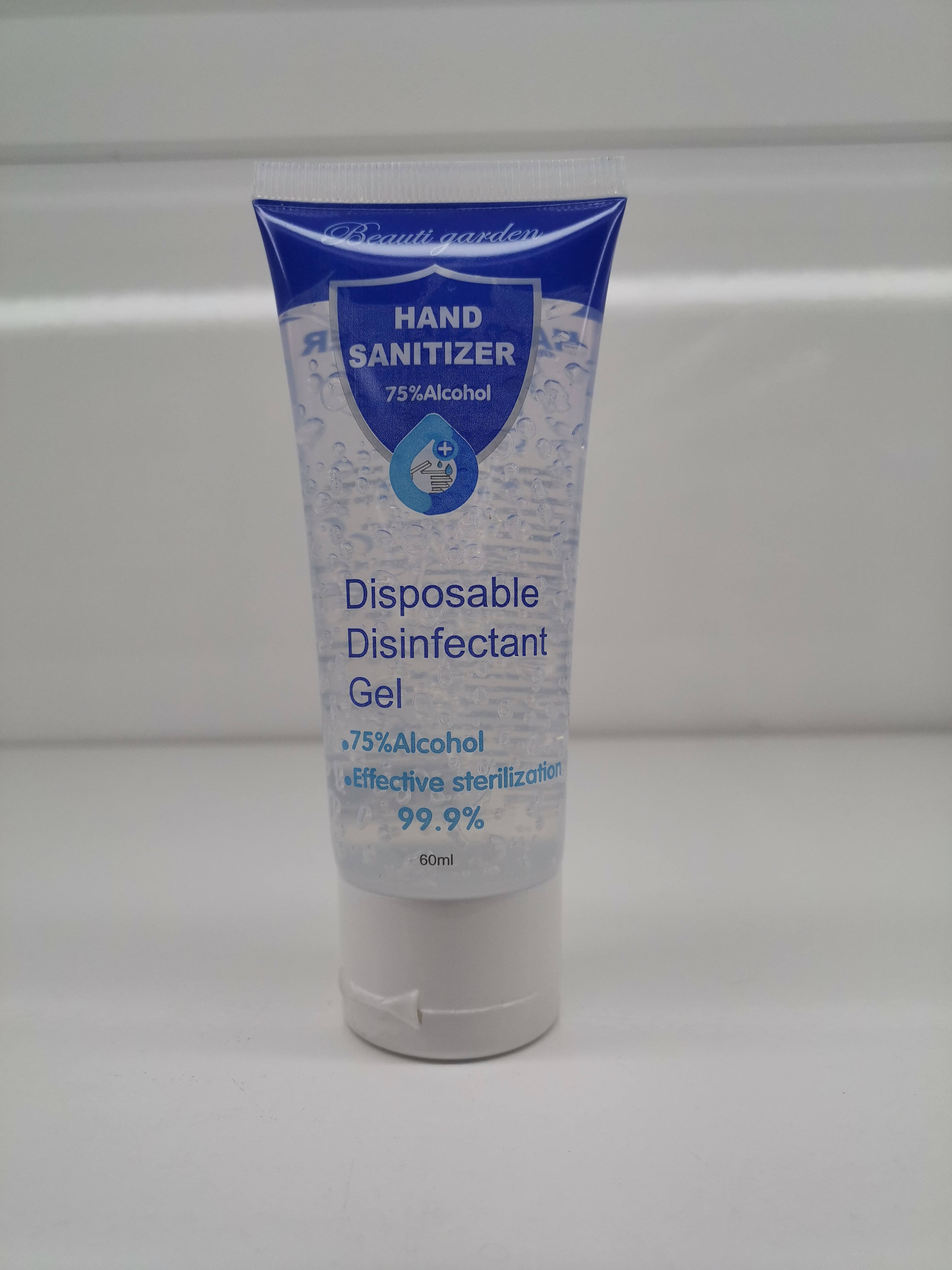 DRUG LABEL: HAND SANITIZER
NDC: 54139-002 | Form: GEL
Manufacturer: YIWU B.GARDEN Cosmetics Co., Ltd.
Category: otc | Type: HUMAN OTC DRUG LABEL
Date: 20200609

ACTIVE INGREDIENTS: ALCOHOL 45 mL/60 mL
INACTIVE INGREDIENTS: AMINOMETHYLPROPANOL; CARBOMER HOMOPOLYMER, UNSPECIFIED TYPE; .ALPHA.-TOCOPHEROL SUCCINATE, D-; WATER

DOSAGE AND ADMINISTRATION

Do not store above 110°F

INACTIVE INGREDIENT

AQUA、CARBOMER、AMINOMETHYL PROPANOL 、VITAMINE

INDICATIONS AND USAGE

Put a thumbnail size amount in your palm and rub Your hands together brisyly until dry

ACTIVE INGREDIENT

ALCOHOL

keep out of reach of children

PURPOSE

Disinfection
Sterilization
No Rinseing

WARNINGS

1.For external use only

2.Flammable. Keep awayfrom fire or flame .When using this product do not use in or near the eyes. In case of contact,rinse eyes thoroughly With water.
3.Stop use and ask a doctor if iritation or rash appears and lasts

4.Keep out of reach of children.
5.If swallowed.get medical help or contact a Poison Control Center right away.